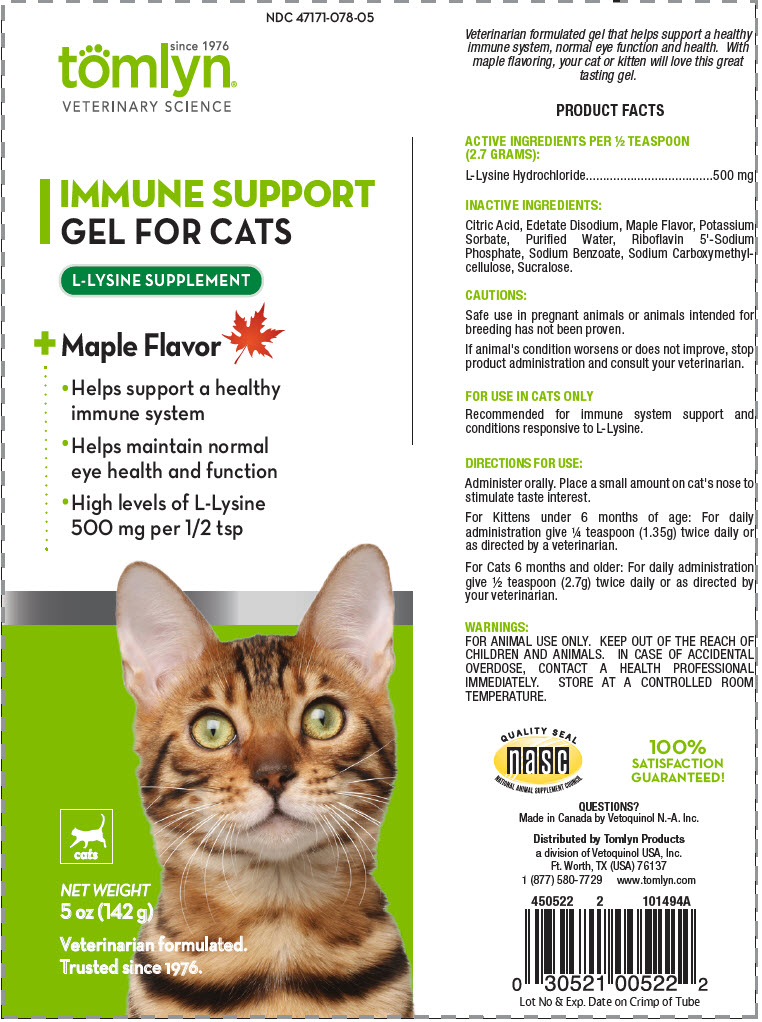 DRUG LABEL: IMMUNE SUPPORT
NDC: 47171-078 | Form: GEL
Manufacturer: Tomlyn Products, a Divison of Vetoquinol USA, Inc.
Category: animal | Type: OTC ANIMAL DRUG LABEL
Date: 20200213

ACTIVE INGREDIENTS: LYSINE HYDROCHLORIDE 185.18 mg/2.7 g
INACTIVE INGREDIENTS: CITRIC ACID MONOHYDRATE; EDETATE DISODIUM; POTASSIUM SORBATE; WATER; RIBOFLAVIN 5'-PHOSPHATE SODIUM ANHYDROUS; SODIUM BENZOATE; CARBOXYMETHYLCELLULOSE SODIUM, UNSPECIFIED FORM; SUCRALOSE

IMMUNE SUPPORT

VETERINARY INDICATIONS

Veterinarian formulated gel that helps support a healthy immune system, normal eye function and health. With maple flavoring, your cat or kitten will love this great tasting gel.

PRODUCT FACTS

ACTIVE INGREDIENTS PER ½ TEASPOON (2.7 GRAMS):

L-Lysine Hydrochloride | 500 mg

INACTIVE INGREDIENTS:

Citric Acid, Edetate Disodium, Maple Flavor, Potassium Sorbate, Purified Water, Riboflavin 5'-Sodium Phosphate, Sodium Benzoate, Sodium Carboxymethylcellulose, Sucralose.

CAUTIONS:

Safe use in pregnant animals or animals intended for breeding has not been proven.

If animal's condition worsens or does not improve, stop product administration and consult your veterinarian.

FOR USE IN CATS ONLY

Recommended for immune system support and conditions responsive to L-Lysine.

DIRECTIONS FOR USE:

Administer orally. Place a small amount on cat's nose to stimulate taste interest.

For Kittens under 6 months of age: For daily administration give ¼ teaspoon (1.35g) twice daily or as directed by a veterinarian.

For Cats 6 months and older: For daily administration give ½ teaspoon (2.7g) twice daily or as directed by your veterinarian.

WARNINGS:

FOR ANIMAL USE ONLY. KEEP OUT OF THE REACH OF CHILDREN AND ANIMALS. IN CASE OF ACCIDENTAL OVERDOSE, CONTACT A HEALTH PROFESSIONAL IMMEDIATELY. STORE AT A CONTROLLED ROOM TEMPERATURE.

QUALITY SEAL
nasc
NATIONAL ANIMAL SUPPLEMENT COUNCIL

100%
SATISFACTION
GUARANTEED!

QUESTIONS?

Made in Canada by Vetoquinol N.-A. Inc.

Distributed by Tomlyn Products
a division of Vetoquinol USA, Inc.
Ft. Worth, TX (USA) 76137
1 (877) 580-7729 www.tomlyn.com

Lot No & Exp. Date on Crimp of Tube

PRINCIPAL DISPLAY PANEL - 142 g Tube Label

NDC 47171-078-05

since 1976
tomlyn®
VETERINARY SCIENCE

IMMUNE SUPPORT
GEL FOR CATS

L-LYSINE SUPPLEMENT

+ Maple Flavor

- Helps support a healthy
  immune system
- Helps maintain normal
  eye health and function
- High levels of L-Lysine
  500 mg per 1/2 tsp

cats

NET WEIGHT
5 oz (142 g)

Veterinarian formulated.
Trusted since 1976.